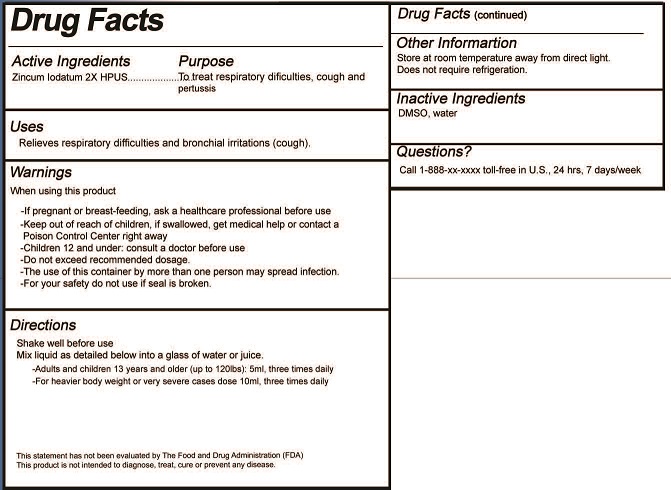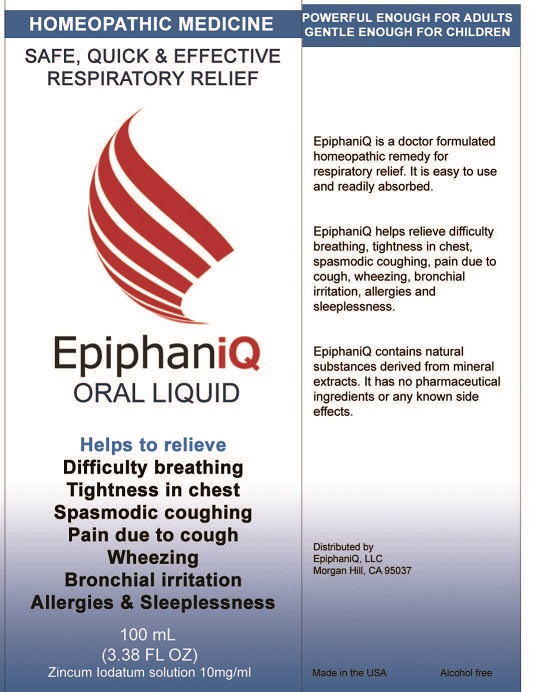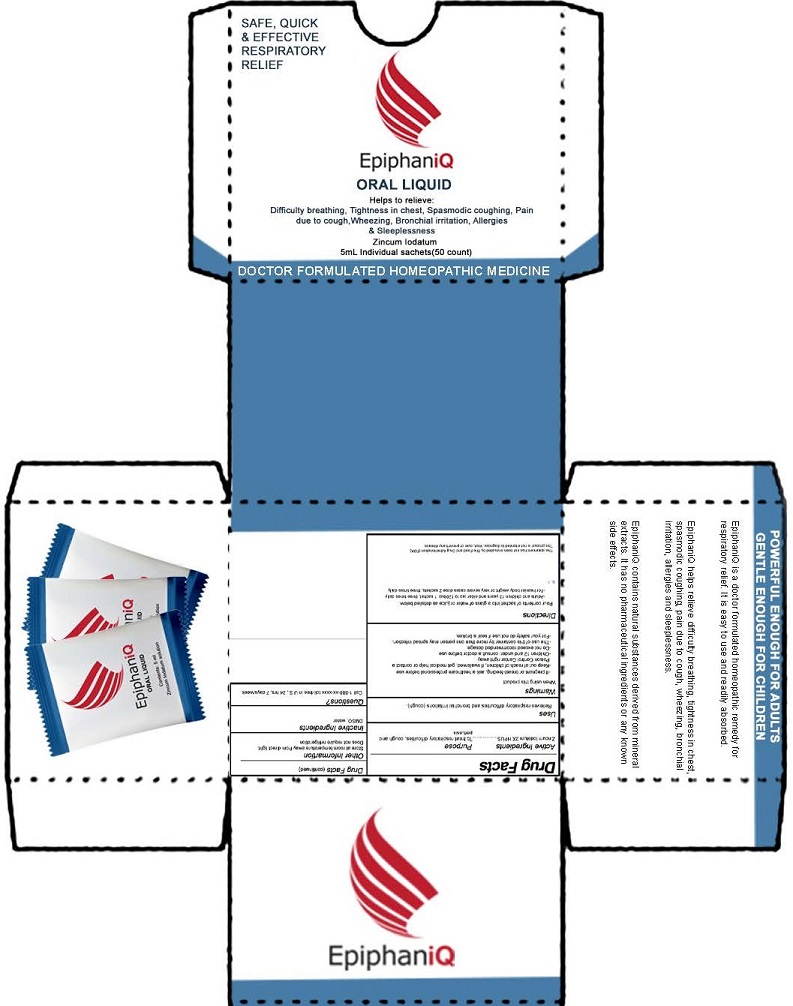 DRUG LABEL: EpiphaniQ
NDC: 79813-204 | Form: SOLUTION
Manufacturer: EpiphaniQ LLC
Category: homeopathic | Type: HUMAN OTC DRUG LABEL
Date: 20211229

ACTIVE INGREDIENTS: ZINC IODIDE 2 [hp_X]/100 mL
INACTIVE INGREDIENTS: DIMETHYL SULFOXIDE; WATER

EpiphaniQ Oral Solution (79813-204)

ACTIVE INGREDIENT

ZINCUM IODATUM 2X HPUS

PURPOSE

TO TREAT RESPIRATORY DIFFICULTIES, COUGH AND PERTUSSIS

USES

Relieves respiratory difficulties and bronchial irritations (cough).

WARNINGS

- If pregnant or breast-feeding ask a healthcare professional before use
- Children under 12: consult a doctor before use
- Do not exceed recommended dosage
- The use of this container by more than one person may spread infection
- For your safety do not use if seal is broken

- Keep out of reach of children. In case of overdose, get medical help or contact a Poison Control center right away

DIRECTIONS

Oral Liquid:

Shake well before use.

Mix liquid as detailed below into a glass of water or juice.

- Adults and children 13 years and older (up to 120lbs): 5ml, three times daily
- For heavier body weight or very severe cases dose 10ml, three times daily

Sachet:

Pour contents of sachets into a glass of water or juice as detailed below

- Adults and children 13 years and older (up to 120lbs): 1 sachet, three times daily
- For heavier body weight or very severe cases dose 2 sachets, three times daily

INACTIVE INGREDIENTS

DMSO, WATER

QUESTIONS

CALL TOLL FREE 1-800-XXX-XXXX IN THE U.S., 24 HRS, 7 DAY/WEEK